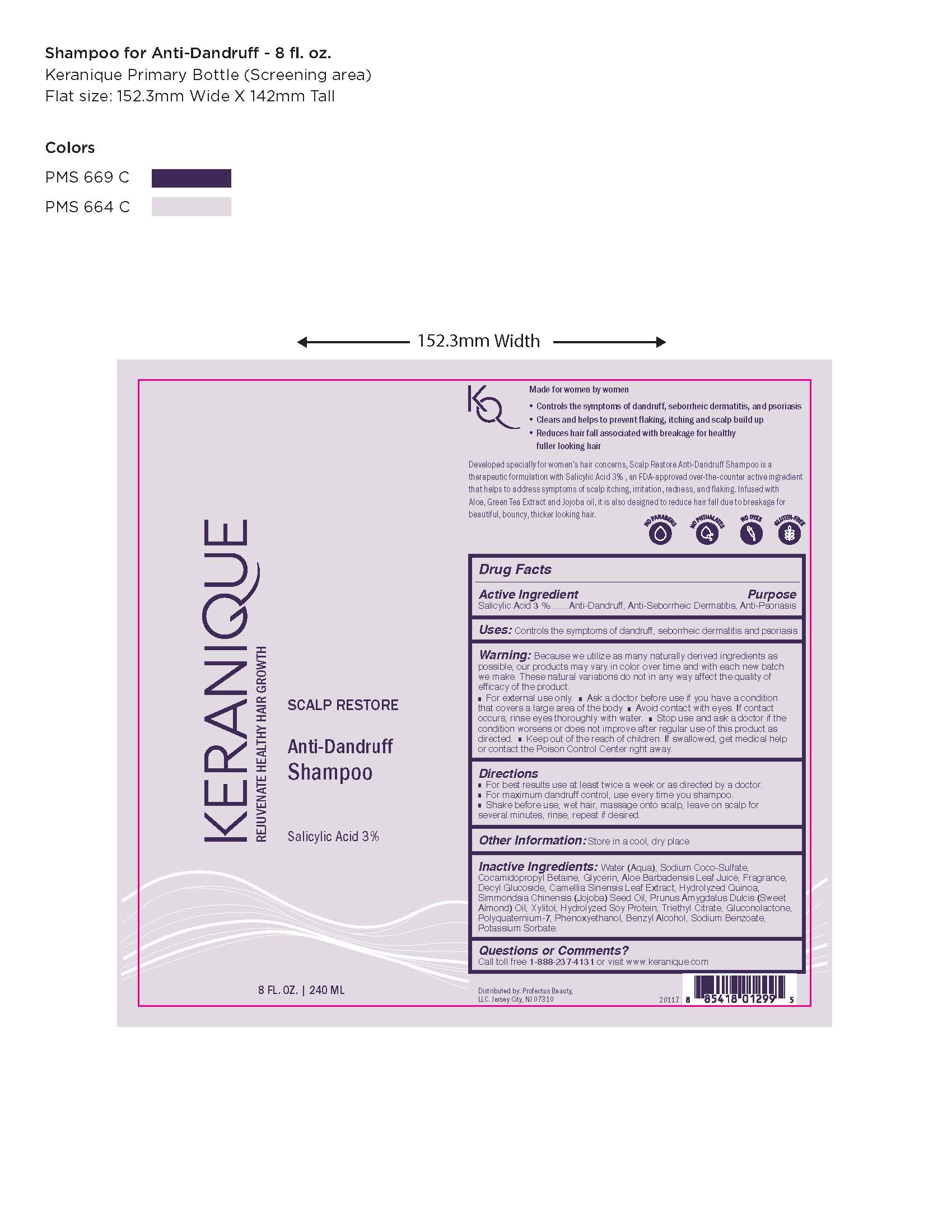 DRUG LABEL: Anti Dandruff
NDC: 70550-329 | Form: LOTION
Manufacturer: Profectus Beauty, LLC
Category: otc | Type: HUMAN OTC DRUG LABEL
Date: 20221106

ACTIVE INGREDIENTS: SALICYLIC ACID 3 g/100 mL
INACTIVE INGREDIENTS: WATER; SODIUM COCO-SULFATE; COCAMIDOPROPYL BETAINE; GLYCINE; ALOE VERA LEAF; DECYL GLUCOSIDE; CAMELLIA SINENSIS WHOLE; SIMMONDSIA CHINENSIS WHOLE; PRUNUS DULCIS WHOLE; XYLITOL; PHENOXYETHANOL; HYDROLYZED SOY PROTEIN (ENZYMATIC; 2000 MW); TRIETHYL CITRATE; GLUCONOLACTONE; POLYQUATERNIUM-7 (70/30 ACRYLAMIDE/DADMAC; 1600 KD); BENZYL ALCOHOL; SODIUM BENZOATE; POTASSIUM SORBATE

DRUG FACTS

Active Ingredients

Salicylic Acid 3.0%

Uses

Controls the symptoms of dandruff, seborrheic dermatitis and psoriasis

Purpose

Anti-Dandruff, Anti-Seborrheic Dermatitis, Anti-Psoriasis

Warnings

Because we utilize as many naturally derived ingredients as
possible, our products may vary in color over time and with each new batch
we make. These natural variations do not in any way affect the quality of
efficacy of the product.
█ For external use only. █ Ask a doctor before use if you have a condition
that covers a large area of the body █ Avoid contact with eyes. If contact
occurs, rinse eyes thoroughly with water. █ Stop use and ask a doctor if the
condition worsens or does not improve after regular use of this product as
directed.

Keep out of reach of children.

█ Keep out of the reach of children. If swallowed, get medical help
or contact the Poison Control Center right away.

Directions

█ For best results use at least twice a week or as directed by a doctor.
█ For maximum dandruff control, use every time you shampoo.
█ Shake before use, wet hair, massage onto scalp, leave on scalp for
several minutes, rinse, repeat if desired.

Other Information

Store in a cool, dry place

Inactive Ingredients

Water (Aqua), Sodium Coco-Sulfate,
Cocamidopropyl Betaine, Glycerin, Aloe Barbadensis Leaf Juice, Fragrance,
Decyl Glucoside, Camellia Sinensis Leaf Extract, Hydrolyzed Quinoa,
Simmondsia Chinensis (Jojoba) Seed Oil, Prunus Amygdalus Dulcis (Sweet
Almond) Oil, Xylitol, Hydrolyzed Soy Protein, Triethyl Citrate, Gluconolactone,
Polyquaternium-7, Phenoxyethanol, Benzyl Alcohol, Sodium Benzoate,
Potassium Sorbate.

Questions or Comments?

Call toll free 1-888-237-4131 or visit www.keranique.com